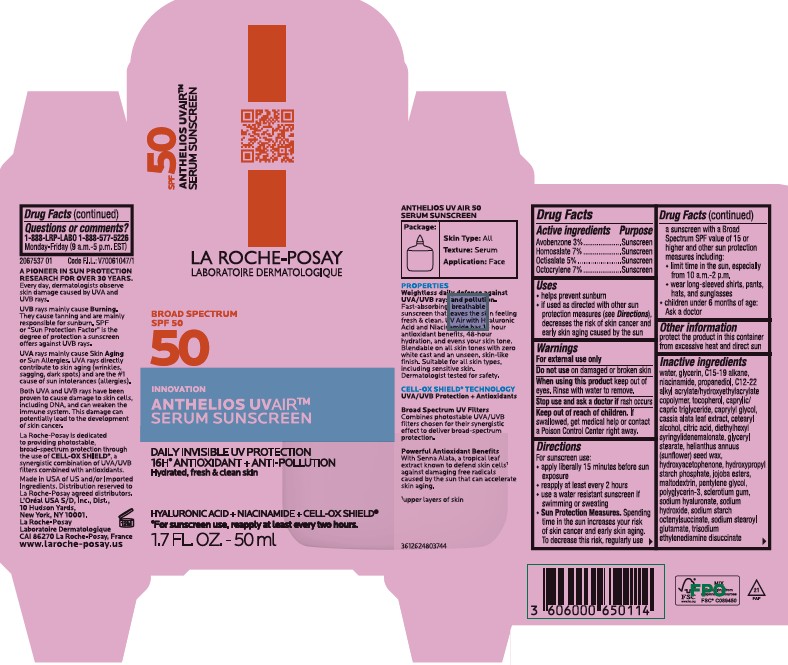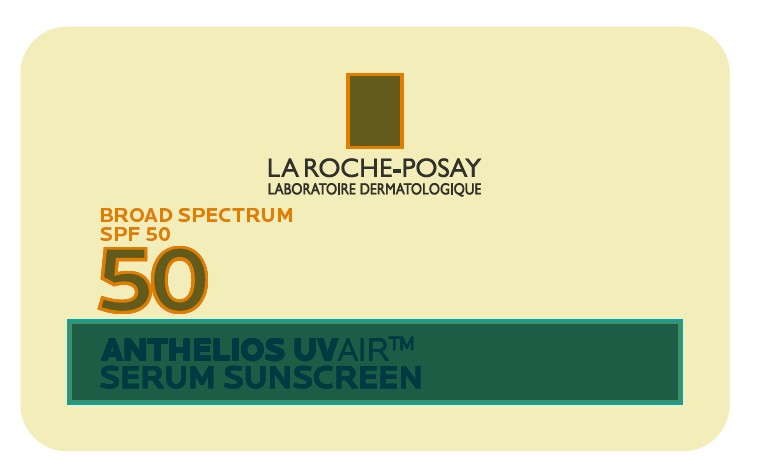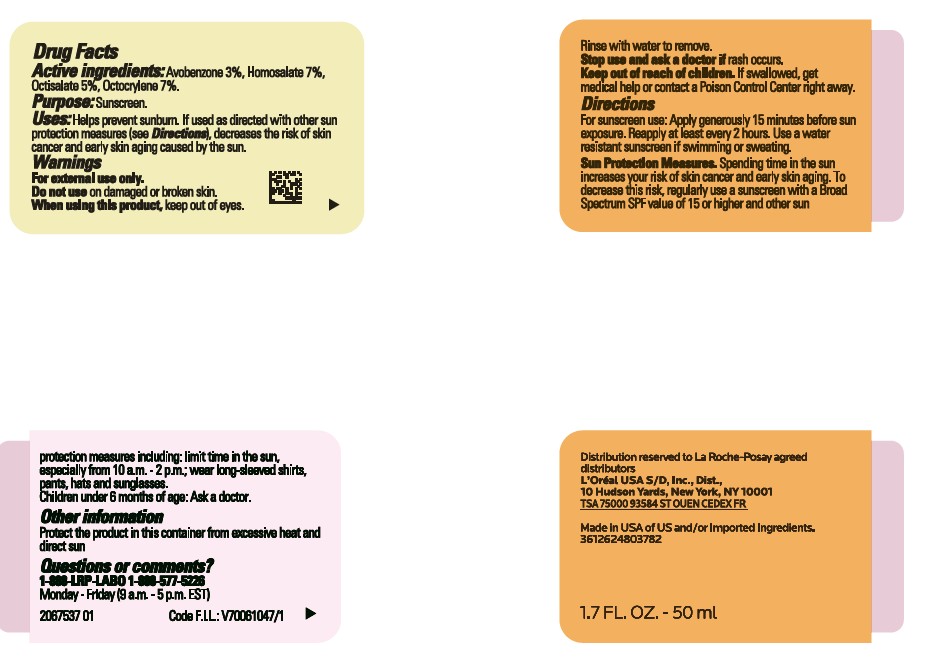 DRUG LABEL: La Roche Posay Anthelios UV Air Serum Sunscreen Broad Spectrum SPF 50
NDC: 82046-114 | Form: LIQUID
Manufacturer: L'Oreal USA Products Inc
Category: otc | Type: HUMAN OTC DRUG LABEL
Date: 20251210

ACTIVE INGREDIENTS: AVOBENZONE 30 mg/1 mL; HOMOSALATE 70 mg/1 mL; OCTISALATE 50 mg/1 mL; OCTOCRYLENE 70 mg/1 mL
INACTIVE INGREDIENTS: WATER; GLYCERIN; C15-19 ALKANE; NIACINAMIDE; PROPANEDIOL; TOCOPHEROL; CAPRYLIC/CAPRIC TRIGLYCERIDE; CAPRYLYL GLYCOL; CETEARYL ALCOHOL; CITRIC ACID; DIETHYLHEXYL SYRINGYLIDENEMALONATE; GLYCERYL STEARATE; HELIANTHUS ANNUUS (SUNFLOWER) SEED WAX; HYDROXYACETOPHENONE; HYDROLYZED JOJOBA ESTERS; MALTODEXTRIN; PENTYLENE GLYCOL; POLYGLYCERIN-3; SCLEROTIUM GUM; SODIUM HYALURONATE; SODIUM HYDROXIDE; SODIUM STEAROYL GLUTAMATE; TRISODIUM ETHYLENEDIAMINE DISUCCINATE

Drug Facts

Active ingredients

Avobenzone 3%

Homosalate 7%

Octisalate 5%

Octocrylene 7%

Purpose

Sunscreen

Uses

- helps prevent sunburn

- if used as directed with other sun protection measures (see Directions), decreases the risk of skin cancer and early skin aging caused by the sun

Warnings

For external use only

Do not use

on damaged or broken skin

When using this product

keep out of eyes. Rinse with water to remove.

Stop use and ask a doctor if

rash occurs

Keep out of reach of children.

If swallowed, get medical help or contact a Poison Control Center right away.

Directions

For sunscreen use:

● apply generously 15 minutes before sun exposure

● reapply at least every 2 hours

● use a water resistant sunscreen if swimming or sweating

● Sun Protection Measures. Spending time in the sun increases your risk of skin cancer and early skin aging. To decrease this risk, regularly use a sunscreen with a Broad Spectrum SPF value of 15 or higher and other sun protection measures including:

● limit time in the sun, especially from 10 a.m. – 2 p.m.

● wear long-sleeved shirts, pants, hats, and sunglasses

● children under 6 months of age: Ask a doctor

Other information

protect the product in this container from excessive heat and direct sun

Inactive ingredients

water, glycerin, C15-19 alkane, niacinamide, propanediol, C12-22 alkyl acrylate/hydroxyethylacrylate copolymer, tocopherol, caprylic/ capric triglyceride, caprylyl glycol, cassia alata leaf extract, cetearyl alcohol, citric acid, diethylhexyl syringylidenemalonate, glyceryl stearate, helianthus annuus (sunflower) seed wax, hydroxyacetophenone, hydroxypropyl starch phosphate, jojoba esters, maltodextrin, pentylene glycol, polyglycerin-3, sclerotium gum, sodium hyaluronate, sodium hydroxide, sodium starch octenylsuccinate, sodium stearoyl glutamate, trisodium ethylenediamine disuccinate

Questions or comments?

1-888-LRP-LAB0 1-888-577-5226

Monday - Friday (9 a.m. - 5 p.m. EST)